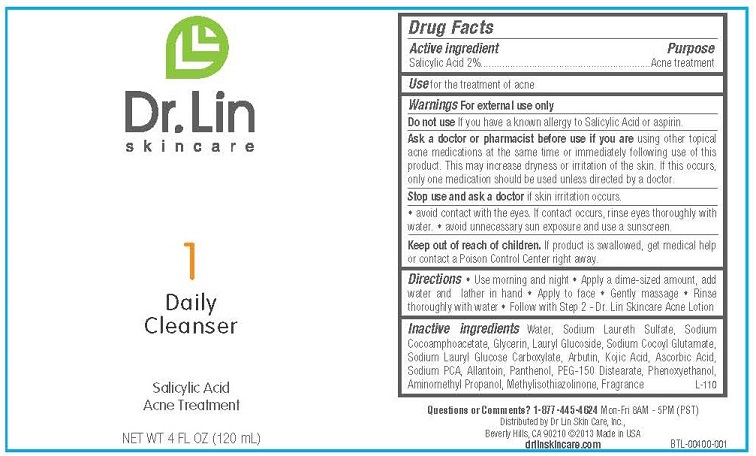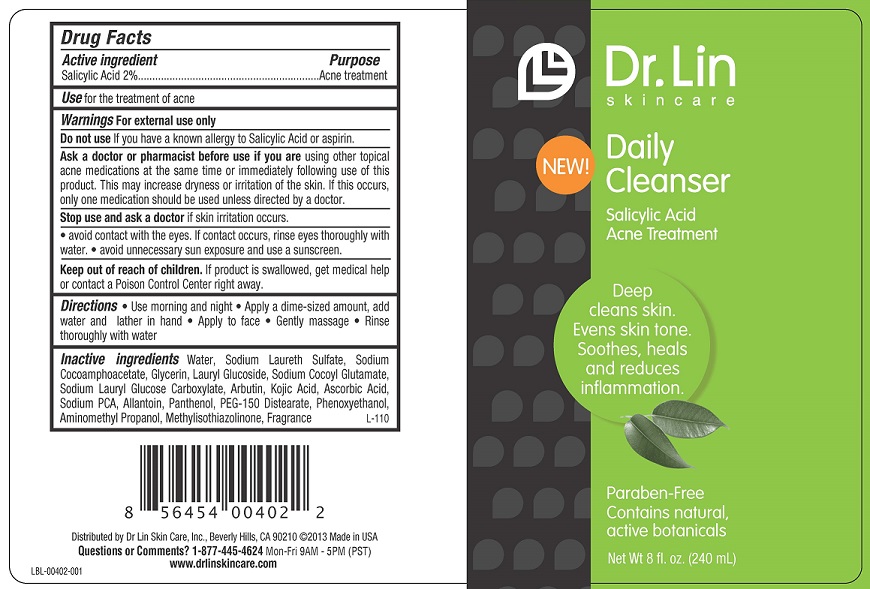 DRUG LABEL: DAILY CLEANSER
NDC: 58876-101 | Form: GEL
Manufacturer: DR LIN SKINCARE
Category: otc | Type: HUMAN OTC DRUG LABEL
Date: 20130617

ACTIVE INGREDIENTS: SALICYLIC ACID 2 g/100 mL
INACTIVE INGREDIENTS: WATER; SODIUM LAURETH SULFATE; SODIUM COCOAMPHOACETATE; GLYCERIN; LAURYL GLUCOSIDE; SODIUM COCOYL GLUTAMATE; SODIUM LAURYL GLYCOL CARBOXYLATE; ARBUTIN; KOJIC ACID; ASCORBIC ACID; SODIUM PYRROLIDONE CARBOXYLATE; ALLANTOIN; PANTHENOL; PEG-150 DISTEARATE; PHENOXYETHANOL; AMINOMETHYLPROPANOL; METHYLISOTHIAZOLINONE

ACTIVE INGREDIENT

SALICYLIC ACID 2%

PURPOSE

ACNE TREATMENT

USE

FOR THE TREATMENT OF ACNE

WARNINGS

FOR EXTERNAL USE ONLY

DO NOT USE IF YOU HAVE A KNOWN SENSITIVITY TO SALICYLIC ACID OR ASPERIN.

ASK A DOCTOR OR PHARMACIST BEFORE USE IF YOU ARE USING OTHER TOPICAL ACNE MEDICATIONS AT THE SAME TIME OR IMMEDIATELY FOLLOWING USE OF THIS PRODUCT. THIS MAY INCREASE DRYNESS OR IRRITATION OF THE SKIN. IF THIS OCCURS, ONLY ONE MEDICATION SHOULD BE USED UNLESS DIRECTED BY A DOCTOR.

STOP USE AND ASK A DOCTOR IF SKIN IRRITATION OCCURS.

- AVOID CONTACT WITH THE EYES. IF CONTACT OCCURS, RINSE EYES THOROUGHLY WITH WATER.
- AVOID UNNECESSARY SUN EXPOSURE AND USE A SUNSCREEN.

KEEP OUT OF REACH OF CHILDREN. IF PRODUCT IS SWALLOWED, GET MEDICL HELP OR CONTACT A POISON CONTROL CENTER RIGHT AWAY.

DIRECTIONS

- USE MORNING AND NIGHT
- APPLY A DIME-SIZED AMOUNT, ADD WATER AND LATHER IN HAND
- APPLY TO FACE
- GENTLY MASSAGE
- RINSE THOROUGHLY WITH WATER

INACTIVE INGREDIENTS

Water, Sodium Laureth Sulfate, Sodium Cocoamphoacetate, Glycerin, Lauryl Glucoside, Sodium Cocoyl Glutamate, Sodium Lauryl Glucose Carboxylate, Arbutin, Kojic Acid, Ascorbic Acid, Sodium PCA, Allantoin, Panthenol, PEG-150 Distearate, Phenoxyethanol, Aminomethyl Propanol, Methylisothiazolinone, Fragrance

QUESTIONS OR COMMENTS? 1-877-445-4624 MON-FRI 8AM - 5PM (PST)